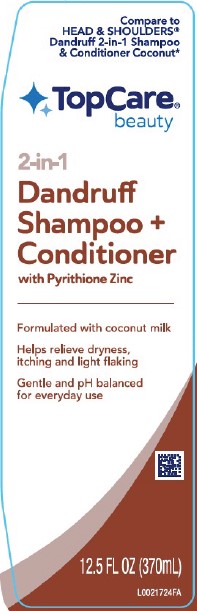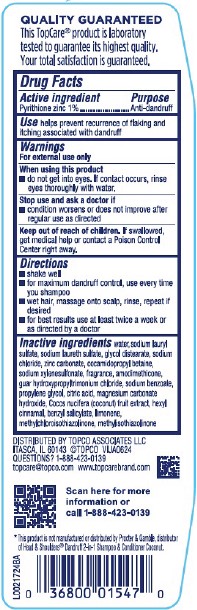 DRUG LABEL: 2 in 1 Dandruff
NDC: 76162-362 | Form: SHAMPOO
Manufacturer: Topco Associates LLC
Category: otc | Type: HUMAN OTC DRUG LABEL
Date: 20260213

ACTIVE INGREDIENTS: PYRITHIONE ZINC 10 mg/1 mL
INACTIVE INGREDIENTS: SODIUM CHLORIDE; ZINC CARBONATE; COCAMIDOPROPYL BETAINE; SODIUM XYLENESULFONATE; AMODIMETHICONE (800 CST); GUAR HYDROXYPROPYLTRIMONIUM CHLORIDE (1.7 SUBSTITUENTS PER SACCHARIDE); SODIUM BENZOATE; PROPYLENE GLYCOL; CITRIC ACID MONOHYDRATE; MAGNESIUM CARBONATE HYDROXIDE; COCONUT; WATER; SODIUM LAURYL SULFATE; SODIUM LAURETH SULFATE; GLYCOL DISTEARATE; HEXYL CINNAMATE; BENZYL SALICYLATE; LIMONENE, (+)-; METHYLCHLOROISOTHIAZOLINONE; METHYLISOTHIAZOLINONE

Top Care 362.000/362AA-AB
Coconut Dandruff 2 in 1 Shampoo & Conditioner

Claims

QUALITY GUARANTEED

This Top Care® porduct is laboratory tested to guarantee its highest quality.

Your total satisfaction is guaranteed.

Active ingredient

Pyrithione zinc 1%

Purpose

Anti-dandruff

Use

helps prevent recurrence of flaking and itching associated with dandruff

Warnings

For external use only

When using this product

- do not get into eyes. If contact occurs, rinse eyes thoroughly with water.

Stop use and ask a doctor if

- condition worsens or does not improve after regular use as directed

Keep out of reach of children.

If swallowed, get medical help or contact a Poison Control Center right away.

Directions

- shake well
- for maximum dandruff control, use every time you shampoo
- wet hair, massage onto scalp, rinse, repeat if desired
- for best results use at least twice a week or as directed by a doctor

Inactive ingredients

water, sodium lauryl sulfate, sodium laureth sulfate, glycol distearate, sodium chloride, zinc carbonate, cocamidopropyl betaine, sodium xylenesulfonate, fragrance, amodimethicone, guar hydroxypropyltrimonium chloride, sodium benzoate, propylene glycol, citric acid, magnesium carbonate hydroxide, Cocos nucifera (coconut) fruit extract, hexyl cinnamal, benzyl salicylate, limonene, methylchloroisothiazolinone, methylisothiazolinone

Adverse Reactions

DISTRIBUTED BY TOPCO ASSOCIATES LLC

ITASCA, IL 60143 © TOPCO VIJA0624

QUESTIONS? 1-888-423-0139

topcare@topco.com www.topcarebrand.com

Scan here for more information or call 1-888-423-0139

Disclaimers

*This product is not manufactured or distributed by Procter & Gamble, distributor of Head & Shoulders® Dandruff 2-in-1 Shampoo & Conditioner Coconut.

Principal Panel Display

Compares to HEAD & SHOULDERS®Dandruff 2-in-1 Shampoo & Conditioner Coconut*

Top Care®

beauty

2-in-1

Dandruff Shampoo + Conditioner

with Pyrithione Zinc

Formulated with coconut milk

Helps relieve dryness, itching and light flaking

Gentle and pH balanced for everyday use

12.5 FL OZ (370 mL)